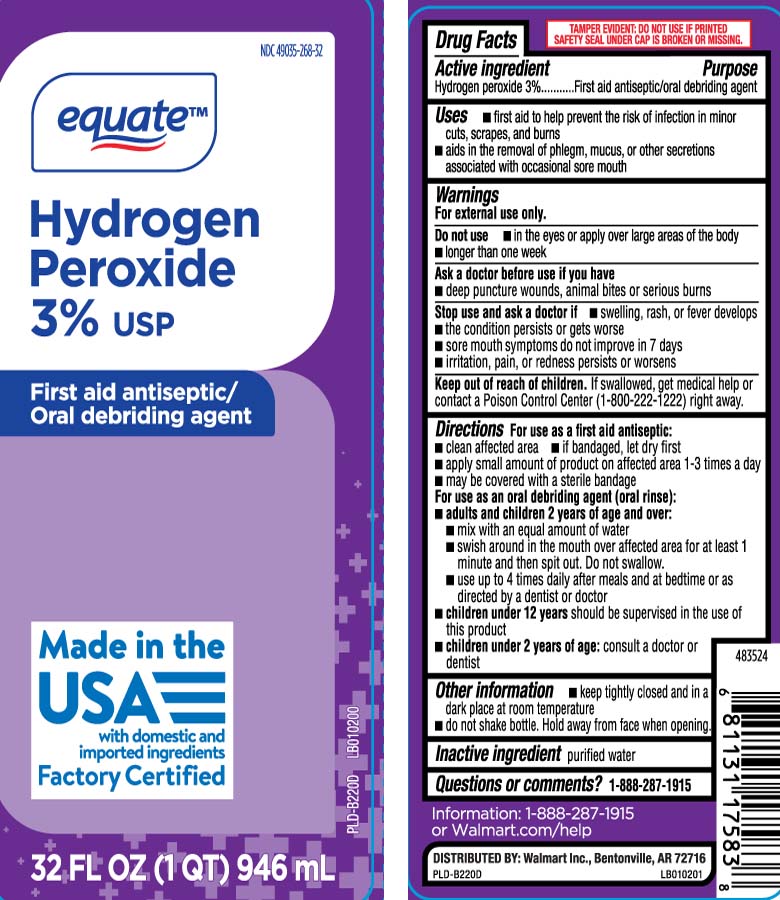 DRUG LABEL: Hydrogen Peroxide
NDC: 49035-268 | Form: LIQUID
Manufacturer: EQUATE (Wal-Mart Stores, Inc.) (see also WAL-MART INC)
Category: otc | Type: HUMAN OTC DRUG LABEL
Date: 20260206

ACTIVE INGREDIENTS: HYDROGEN PEROXIDE 2.65 mL/100 mL
INACTIVE INGREDIENTS: WATER

Drug Facts

Active ingredient

Hydrogen peroxide 3%

Purpose

first aid antiseptic/oral debriding agent

Uses

- first aid to help prevent the risk of infection in minor cuts, scrapes and burns
- aids in the removal of phlegm, mucus, or other secretions associated with occasional sore mouth

Warnings

For external use only.

Do not use

- in the eyes or apply over large areas of the body
- longer than one week

Ask a doctor before use if you have

- deep or puncture wounds, animal bites or serious burns

Stop use and ask a doctor if

- swelling, rash, or fever develops
- the condition persists or gets worse
- sore mouth symptoms do not improve in 7 days
- irritation, pain or redness persists or worsens

Keep out of reach of children.

If swallowed, get medical help or contact a Poison Control Center (1-800-222-1222) right away.

Directions

For use as a first aid antiseptic:

- clean affected area
- if bandaged, let dry first
- apply small amount of product on affected area 1-3 times a day
- may be covered with a sterile bandage

For use as an oral debriding agent (oral rinse):

- adults and children 2 years of age and over:
- mix with an equal amount of water
- swish around in the mouth over affected area for at least 1 minute and then spit out. Do not swallow.
- use up to 4 times daily after meals and at bedtime or as directed by a dentist or doctor
- children under 12 years should be supervised in the use of this product
- children under 2 years of age: consult a dentist or doctor

Other information

- Keep tightly closed and in a dark place at room temperature.
- Do not shake bottle. Hold away from face when opening.

Inactive ingredient

purified water

Questions or comments?

1-888-287-1915

Princiapl Display Panel

Hydrogen Peroxide 3% USP

First aid Antiseptic/

Oral debriding agent

FL OZ (mL)

TAMPER EVIDENT: DO NOT USE IF PRINTED SAFETY SEAL UNDER CAP IS BROKEN OR MISSING.

DISTRIBUTED BY: Walmart Inc.,

Bentonville, AR 72716

Package Label

EQUATE Hydrogen Peroxide 3% USP